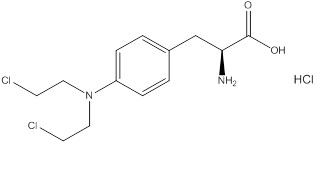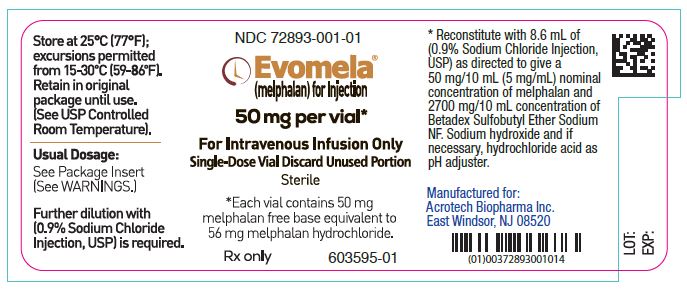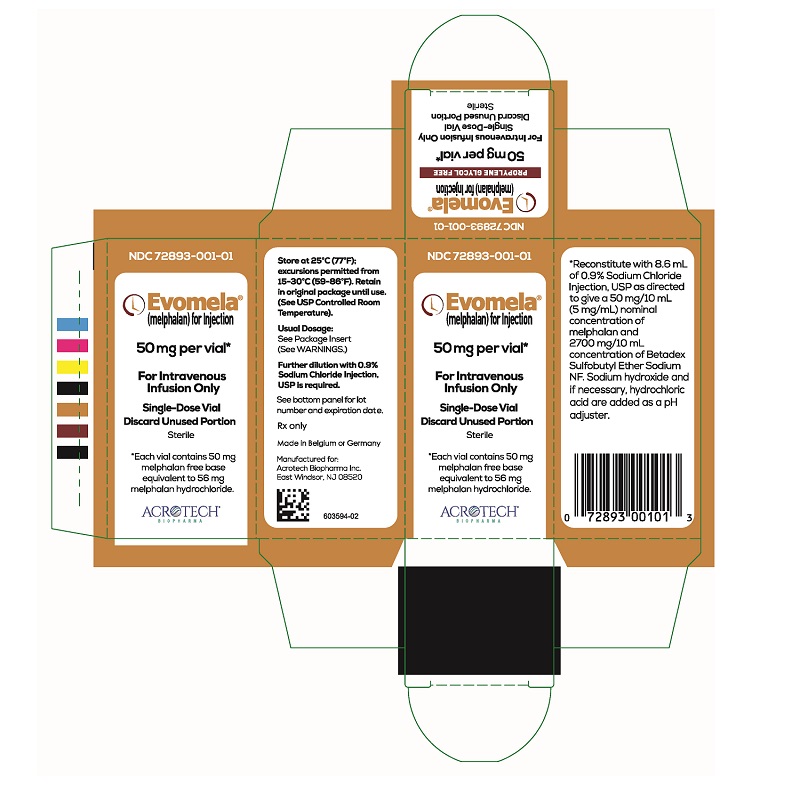 DRUG LABEL: EVOMELA
NDC: 72893-001 | Form: INJECTION, POWDER, LYOPHILIZED, FOR SOLUTION
Manufacturer: Acrotech Biopharma Inc
Category: prescription | Type: Human Prescription Drug Label
Date: 20230613

ACTIVE INGREDIENTS: MELPHALAN HYDROCHLORIDE 50 mg/10 mL
INACTIVE INGREDIENTS: BETADEX SULFOBUTYL ETHER SODIUM 2700 mg/10 mL

HIGHLIGHTS OF PRESCRIBING INFORMATION

These highlights do not include all the information needed to use EVOMELA® safely and effectively. See full prescribing information for EVOMELA.
EVOMELA (melphalan) for injection, for intravenous use.
Initial U.S. Approval: 1964

RECENT MAJOR CHANGES

Indications and Usage, Palliative Treatment (1.2) Removed 8/2021
Dosage and Administration (2.2, 2.3, 2.4) 11/2021
Warnings and Precautions (5.1, 5.2) 8/2021

WARNING: SEVERE BONE MARROW SUPPRESSION, HYPERSENSITIVITY, and LEUKEMOGENICITY

See full prescribing information for complete boxed warning.

- Severe bone marrow suppression with resulting infection or bleeding may occur. Controlled trials comparing intravenous (IV) melphalan to oral melphalan have shown more myelosuppression with the IV formulation. Monitor hematologic laboratory parameters. (5.1)

- Hypersensitivity reactions, including anaphylaxis, have occurred in approximately 2% of patients who received the IV formulation of melphalan. Discontinue treatment with Evomela for serious hypersensitivity reactions. (5.4)

- Melphalan produces chromosomal aberrations in vitro and in vivo. Evomela should be considered potentially leukemogenic in humans. (5.5)

1 INDICATIONS AND USAGE

Evomela is an alkylating drug indicated for use as a high-dose conditioning treatment prior to hematopoietic progenitor (stem) cell transplantation in patients with multiple myeloma. (1.1)

2 DOSAGE AND ADMINISTRATION

For Conditioning Treatment, the recommended dose of Evomela is 100 mg/m^2 /day administered over 30 minutes by intravenous infusion for 2 consecutive days (Day -3 and Day -2) prior to autologous stem cell transplantation (ASCT, Day 0). (2.1)

3 DOSAGE FORMS AND STRENGTHS

For Injection: 50 mg per vial, lyophilized powder in a single-dose vial for reconstitution. (3)

4 CONTRAINDICATIONS

History of serious allergic reaction to melphalan

5 WARNINGS AND PRECAUTIONS

- Gastrointestinal toxicity: Nausea, vomiting, diarrhea or oral mucositis may occur; provide supportive care using antiemetic and antidiarrheal medications as needed. (2.1, 5.2)

- Embryo-fetal toxicity: Can cause fetal harm. Advise females of reproductive potential and males with female partners of reproductive potential of the potential risk to a fetus and to use effective contraception. (5.6, 8.1, 8.3)

- Infertility: Melphalan may cause ovarian function suppression or testicular suppression. (5.7)

6 ADVERSE REACTIONS

Most common adverse reactions observed in at least 50% of patients treated with Evomela are neutrophil count decreased, white blood cell count decreased, lymphocyte count decreased, platelet count decreased, diarrhea, nausea, fatigue, hypokalemia, anemia, and vomiting. (6.1)

To report SUSPECTED ADVERSE REACTIONS, contact Acrotech Biopharma Inc. at 1-888-292-9617 or FDA at 1-800-FDA-1088 or www.fda.gov/medwatch

8 USE IN SPECIFIC POPULATIONS

- Lactation: Advise not to breastfeed (8.2)

FULL PRESCRIBING INFORMATION

WARNING: SEVERE BONE MARROW SUPPRESSION, HYPERSENSITIVITY, and LEUKEMOGENICITY

- Severe bone marrow suppression with resulting infection or bleeding may occur. Controlled trials comparing intravenous (IV) melphalan to oral melphalan have shown more myelosuppression with the IV formulation. Monitor hematologic laboratory parameters. [see Warnings and Precautions (5.1)]

- Hypersensitivity reactions, including anaphylaxis, have occurred in approximately 2% of patients who received the IV formulation of melphalan. Discontinue treatment with Evomela for serious hypersensitivity reactions. [see Warnings and Precautions (5.4)]

- Melphalan produces chromosomal aberrations in vitro and in vivo. Evomela should be considered potentially leukemogenic in humans. [see Warnings and Precautions (5.5)]

1 INDICATIONS AND USAGE

1.1 Multiple Myeloma-Conditioning Treatment

Evomela is indicated for use as a high-dose conditioning treatment prior to hematopoietic progenitor (stem) cell transplantation in patients with multiple myeloma.

2 DOSAGE AND ADMINISTRATION

2.1 Recommended Dosage for Conditioning Treatment

The recommended dose of Evomela for conditioning treatment is 100 mg/m^2/day administered over 30 minutes by intravenous infusion for 2 consecutive days (Day -3 and Day -2) prior to autologous stem cell transplantation (ASCT, Day 0). For patients who weigh more than 130% of their ideal body weight, body surface area should be calculated based on adjusted ideal body weight.

Administer prophylactic antiemetics [see Warnings and Precautions (5.2)].

2.2 Preparation and Administration

Evomela is a hazardous drug. Follow applicable special handling and disposal procedures^1.

Evomela is light sensitive. Retain in original carton until use.

Do not mix Evomela with other melphalan hydrochloride for injection drug products.

Reconstitution and Infusion Instructions:

1. Use 0.9% Sodium Chloride Injection, USP (8.6 mL as directed) to reconstitute Evomela and make a 50 mg/10 mL (5 mg/ mL) nominal concentration of melphalan.

The reconstituted Evomela drug product is stable for 24 hours at refrigerated temperature (5oC) without any precipitation due to the high solubility.

The reconstituted Evomela drug product is stable for 1 hour at room temperature.

2. Calculate the required volume of Evomela needed for a patient’s dose and withdraw that volume from the vial(s).

3. Add the required volume of Evomela to the appropriate volume of 0.9% Sodium Chloride Injection, USP to a final concentration of 0.45 mg/mL.
The Evomela admixture solution is stable for 4 hours at room temperature in addition to the 1 hour following reconstitution.
4. Infuse over 30 minutes via an injection port or central venous catheter.
Evomela may cause local tissue damage should extravasation occur. Do not administer by direct injection into a peripheral vein. Administer Evomela by injecting slowly into a fast-running IV infusion via a central venous access line.
Parenteral drug products should be inspected visually for particulate matter and discoloration prior to administration, whenever solution and container permit.

3 DOSAGE FORMS AND STRENGTHS

For injection: 50 mg, white to off-white lyophilized powder in single-dose vial for reconstitution (after reconstitution the solution is clear and colorless to light yellow). Each vial contains 50 mg melphalan free base equivalent to 56 mg melphalan hydrochloride.

4 CONTRAINDICATIONS

History of serious allergic reaction to melphalan.

5 WARNINGS AND PRECAUTIONS

5.1 Bone Marrow Suppression

For patients receiving Evomela as part of a conditioning regimen, myeloablation occurs in all patients. Do not begin the conditioning regimen if a stem cell product is not available for rescue. Monitor complete blood counts, provide supportive care for infections, anemia and thrombocytopenia until there is adequate hematopoietic recovery.

5.2 Gastrointestinal Toxicity

For patients receiving Evomela as part of a conditioning regimen, nausea, vomiting, mucositis, and diarrhea may occur in over 50% of patients. Use prophylactic antiemetic medication. Provide supportive care for nausea, vomiting, diarrhea, and mucositis. The frequency of grade 3/4 mucositis in clinical studies was 13%. Provide nutritional support and analgesics for patients with severe mucositis. [see Dosage and Administration (2.1) and Adverse Reactions (6.1)].

5.3 Hepatotoxicity

Hepatic disorders ranging from abnormal liver function tests to clinical manifestations such as hepatitis and jaundice have been reported after treatment with melphalan. Hepatic veno-occlusive disease has also been reported. Monitor liver chemistries.

5.4 Hypersensitivity

Acute hypersensitivity reactions, including anaphylaxis, have occurred in approximately 2% of patients who received an intravenous formulation of melphalan. Symptoms may include urticaria, pruritus, edema, and skin rashes and, in some patients, tachycardia, bronchospasm, dyspnea, and hypotension. Discontinue treatment with Evomela for serious hypersensitivity reactions.

5.5 Secondary Malignancies

Melphalan has been shown to cause chromatid or chromosome damage in humans. Secondary malignancies such as myeloproliferative syndrome or acute leukemia have been reported in multiple myeloma patients treated with melphalan-containing chemotherapy regimens. The potential benefit of Evomela therapy must be considered against the possible risk of the induction of a secondary malignancy.

5.6 Embryo-Fetal Toxicity

Based on its mechanism of action, Evomela can cause fetal harm when administered to a pregnant woman. Melphalan is genotoxic, targets actively dividing cells, and was embryolethal and teratogenic in rats. Advise pregnant women of the potential risk to a fetus. Advise females of reproductive potential to use effective contraception during treatment with Evomela and for 6 months after the last dose. Advise males with female partners of reproductive potential to use effective contraception during treatment with Evomela and for 3 months after the last dose [see Use in Specific Populations (8.1, 8.3)].

5.7 Infertility

Melphalan-based chemotherapy regimens have been reported to cause suppression of ovarian function in premenopausal women, resulting in persistent amenorrhea in approximately 9% of patients. Reversible or irreversible testicular suppression has also been reported [see Use in Specific Populations (8.3)].

6 ADVERSE REACTIONS

The following serious adverse reactions are described in more detail in other sections of the prescribing information.

- Bone Marrow Suppression [see Warnings and Precautions (5.1)]
- Gastrointestinal Toxicity [see Warnings and Precautions (5.2)]
- Hepatotoxicity [see Warnings and Precautions (5.3)]
- Hypersensitivity [see Warnings and Precautions (5.4)]
- Secondary Malignancies [see Warnings and Precautions (5.5)]

6.1 Clinical Trials Experience

Because clinical studies are conducted under widely varying conditions, adverse reaction rates observed in the clinical studies of Evomela may not reflect the rates observed in practice.

The most common adverse reactions observed in at least 50% of patients with multiple myeloma treated with Evomela were neutrophil count decreased, white blood cell count decreased, lymphocyte count decreased, platelet count decreased, diarrhea, nausea, fatigue, hypokalemia, anemia, and vomiting.

Myeloablative Conditioning in Multiple Myeloma Patients Undergoing ASCT

The safety of Evomela was evaluated in 61 patients with multiple myeloma in a single arm clinical trial in which patients were administered Evomela at a dosage of 100 mg/m^2/day administered over ~30 minutes (range: 24-48 minutes) by intravenous (IV) infusion for 2 consecutive days (Day -3 and Day -2) prior to autologous stem cell transplant (ASCT, Day 0). [see Clinical Studies (14.1)].

Table 1 summarizes the adverse reactions from the single-arm trial in patients with multiple myeloma. Severe myelosuppression is expected and these adverse reactions are not listed below.

Table 1 Non-hematologic Adverse Reactions in≥ 25% of Patients with Multiple Myeloma Who Received Evomela Conditioning for ASCT
Adverse Reactions | Number (%) of Patients (N=61)
Adverse Reactions | All Grades | Grade 3or 4
All Adverse Reactions | 61 | 61
Diarrhea | 57 (93%) | 2 (3%)
Nausea | 55 (90%) | 1 (2%)
Fatigue | 47 (77%) | 1 (2%)
Hypokalemia | 45 (74%) | 17 (28%)
Vomiting | 39 (64%) | 0 (0%)
Hypophosphatemia | 30 (49%) | 29 (2%)
Decreased Appetite | 30 (49%) | 0 (0%)
Pyrexia | 29 (48%) | 2 (3%)
Constipation | 29 (48%) | 0 (0%)
Febrile Neutropenia | 25 (41%) | 17 (28%)
Mucosal Inflammation | 23 (38%) | 6 (10%)
Dizziness | 23 (38%) | 0 (0%)
Edema Peripheral | 20 (33%) | 0 (0%)
Stomatitis | 17 (28%) | 3 (5%)
Abdominal Pain | 17 (28%) | 0 (0%)
Dysgeusia | 17 (28%) | 0 (0%)
Dyspepsia | 16 (26%) | 0 (0%)

Serious Adverse Reactions

Twelve (20%) patients experienced a treatment emergent serious adverse reaction while on study. The most common serious adverse reactions (>1 patient, 1.6%) were pyrexia, hematochezia, febrile neutropenia, and renal failure. Treatment-related serious adverse reactions reported in >1 patient were pyrexia (n=2, 3%), febrile neutropenia (n=2, 3%), and hematochezia (n=2, 3%).

7 DRUG INTERACTIONS

No formal drug interaction studies have been conducted. The development of severe renal impairment has been reported in patients treated with a single dose of intravenous melphalan 140-250 mg/m^2 followed by standard oral doses of cyclosporine. Intravenous melphalan may also reduce the threshold for BCNU lung toxicity.

8 USE IN SPECIFIC POPULATIONS

8.1 Pregnancy

Risk Summary

Based on its mechanism of action, Evomela can cause fetal harm when administered to a pregnant woman, including teratogenicity and/or embryo-fetal lethality [see Clinical Pharmacology (12.1)]. Melphalan is a genotoxic drug and can cause chromatid or chromosome damage in humans [see Nonclinical Toxicology (13.1)]. In animal studies, melphalan was embryolethal and teratogenic in rats at doses below the recommended clinical doses [see Data]. Advise a pregnant woman of the potential risk to a fetus..

The background risk of major birth defects and miscarriage for the indicated populations are unknown. However, the background risk in the U.S. general population of major birth defects is 2-4% and of miscarriage is 15-20% of clinically recognized pregnancies.

Data

Animal Data

Adequate animal studies have not been conducted with intravenous melphalan. Melphalan was embryolethal and teratogenic in rats following oral administration of 6 to 18 mg/m^2/day for 10 days (0.06 to 0.18 times the highest recommended clinical dose of 100 mg/m^2/day) and intraperitoneal administration of 18 mg/m^2 (0.18 times the highest recommended clinical dose). Malformations resulting from melphalan administration included alterations of the brain (underdevelopment, deformation, meningocele, and encephalocele) and eye (anophthalmia and microphthalmos), reduction of the mandible and tail, and hepatocele (exomphaly).

8.2 Lactation

Risk Summary

It is not known whether melphalan is present in human milk. Because many drugs are excreted in human milk and because of the potential for serious adverse reactions in nursing children from melphalan, breastfeeding is not recommended during treatment with Evomela and for one week after the last dose.

8.3 Females and Males of Reproductive Potential

Evomela can cause fetal harm when administered to a pregnant woman [see Use in Specific Populations (8.1)].

Contraception

Females

Advise females of reproductive potential to use effective contraception during treatment with Evomela and for 6 months after the last dose.

Males

Evomela administration may damage spermatozoa and testicular tissue, resulting in possible genetic fetal abnormalities. Advise males with female partners of reproductive potential to use effective contraception during treatment with Evomela and for 3 months after the last dose [see Nonclinical Toxicology (13.1)].

Infertility

Females

Melphalan causes suppression of ovarian function in premenopausal women, resulting in amenorrhea in a significant number of patients.

Males

Reversible and irreversible testicular suppression has been reported in male patients after administration of melphalan.

8.4 Pediatric Use

Pediatric patients were not included in clinical trials. Safety and effectiveness have not been established in pediatric patients.

8.5 Geriatric Use

Of the total number of subjects in the single-arm pivotal study of Evomela, 30% were 65 and over, but no patients were 75 and over. No overall differences in safety or effectiveness were observed between these subjects and younger subjects. A greater incidence of engraftment syndrome was observed in older patients; 7% (3 of 43) of patients younger than 65 years old versus 28% (5 of 18) of patients 65 years old and over.

10 OVERDOSAGE

Overdoses resulting in death have been reported with melphalan. Overdoses, including doses up to 290 mg/m^2, have produced the following symptoms: severe nausea and vomiting, decreased consciousness, convulsions, muscular paralysis, and cholinomimetic effects. Severe mucositis, stomatitis, colitis, diarrhea, and hemorrhage of the gastrointestinal tract occur at high doses (>100 mg/m^2). Elevations in liver enzymes and veno-occlusive disease occur infrequently. Significant hyponatremia, caused by an associated inappropriate secretion of ADH syndrome, has been observed. Nephrotoxicity and adult respiratory distress syndrome have been reported rarely.

The principal toxic effect is bone marrow suppression leading to leucopenia, thrombocytopenia and anemia. Hematologic parameters should be closely followed for 3 to 6 weeks. An uncontrolled study suggests that administration of autologous bone marrow or hematopoietic growth factors (i.e., sargramostim, filgrastim) may shorten the period of pancytopenia. General supportive measures together with appropriate blood transfusions and antibiotics should be instituted as deemed necessary by the physician. This drug is not removed from plasma to any significant degree by hemodialysis or hemoperfusion. A pediatric patient survived a 254 mg/m^2 overdose treated with standard supportive care.

11 DESCRIPTION

Evomela contains melphalan hydrochloride, an alkylating drug, as the active ingredient. The chemical name of melphalan hydrochloride is 4-[bis(2-chloroethyl)amino]-L-phenylalanine hydrochloride. Its molecular formula is C13H18Cl2N2O2 • HCl and the molecular weight is 341.67. The structural formula is:

Melphalan hydrochloride is a white to off-white powder, with a melting range of 199°C − 201°C. It is practically insoluble in water, but freely soluble in 1N HCl and methanol.

Evomela (melphalan) for injection is supplied as a sterile white to off-white lyophilized powder in a single-dose vial for intravenous use. Each vial contains 50 mg melphalan free base equivalent to 56 mg melphalan hydrochloride and 2700 mg Betadex Sulfobutyl Ether Sodium, NF. Sodium hydroxide and if necessary, hydrochloric acid are added as a pH adjuster.

12 CLINICAL PHARMACOLOGY

12.1 Mechanism of Action

Melphalan is an alkylating agent of the bischloroethylamine type. As a result, its cytotoxicity appears to be related to the extent of its interstrand cross-linking with DNA, probably by binding at the N^7 position of guanine. Like other bifunctional alkylating agents, it is active against both resting and rapidly dividing tumor cells.

12.2 Pharmacodynamics

The peak mean heart rate increased 20 bpm from baseline following melphalan 100 mg/m^2 for 2 consecutive days in multiple myeloma patients undergoing autologous stem cell transplantation.

Cardiac Electrophysiology

No large mean increase in QTc (i.e. > 20 ms) was detected following melphalan 100 mg/m^2.

12.3 Pharmacokinetics

Mean (± SD) peak plasma concentrations and AUC0-inf were 5.8 ± 1.5 mcg/mL and 451 ± 109 mcg*min/mL, respectively, following administration of melphalan 100 mg/m^2 in multiple myeloma patients.

Distribution

The volume of distribution of melphalan ranges from approximately 35.5 to 185.7 L/m^2. Melphalan penetrates into cerebrospinal fluid (CSF). Protein binding of melphalan ranges from approximately 50% to 90%, primarily to serum albumin (40% to 60%) and to a lesser extent to α1-acid glycoprotein (20%). Approximately 30% of melphalan is (covalently) irreversibly bound to plasma proteins.

Elimination

Melphalan terminal elimination half-life is approximately 75 minutes. Average total body clearance (CL) ranges from approximately 250 to 325 mL/min/m^2.

Metabolism

Melphalan primarily undergoes chemical hydrolysis to inactive metabolites.

Excretion

Mean values of melphalan excreted in urine range from 5.8% to 21.3%.

Specific Populations

Patient Body Weight

Melphalan clearance changes with ideal body weight (IBW), which decreased by 28% and increased by 31% with IBW of 45 kg and 100 kg compared to 70 kg IBW, respectively.

Renal Impairment

A decrease in estimated creatinine CL from 100 mL/min to 30 mL/min results in 28.2% reduction in CL for a typical person with an IBW of 70 kg.

13 NONCLINICAL TOXICOLOGY

13.1 Carcinogenesis, Mutagenesis, Impairment of Fertility

Adequate and well-controlled carcinogenicity studies have not been conducted in animals. However, intraperitoneal (IP) administration of melphalan in rats (5.4 to 10.8 mg/m^2) and in mice (2.25 to 4.5 mg/m^2) 3 times per week for 6 months followed by 12 months post-dose observation produced peritoneal sarcomas and lung tumors, respectively.

Intramuscular administration of melphalan at 6 and 60 mg/m^2 produced structural aberrations of the chromatid and chromosomes in bone marrow cells of Wistar rats.

14. CLINICAL STUDIES

14.1 Myeloablative Conditioning in Patients with Multiple Myeloma Undergoing ASCT

An open-label, single-arm, non-randomized trial of Evomela was conducted at 5 US centers (NCT 01660633). The 61 patients enrolled had symptomatic multiple myeloma and had at least 2 × 10^6 CD34+ cells/kg cryopreserved stem cells available. The median age was 62 years (range 32 to 73); 57% male, 80% white, 18% black, 2% Asian. Evomela was administered at 100 mg/m^2/day over 30 minutes by IV infusion for two consecutive days (Day -3 and Day -2) prior to ASCT (Day 0).

The objective of the trial was to determine the overall safety and toxicity profile of 200 mg/m^2 of Evomela in patients with multiple myeloma undergoing ASCT.The efficacy was evaluated by the International Myeloma Working Group response criteria comparing the disease response immediately prior to the ASCT procedure to the disease response assessed 90 to 100 days post-transplant. In addition, successful myeloablation, and time to engraftment were evaluated.

The overall response rate (partial response or better) improved from 79% (48 of 61) prior to the ASCT procedure to 95% (58 of 61) at 90 to 100 days post-transplant. There was also an increase in the number of patients with a stringent complete response from 0 patients prior to the ASCT procedure to 16% (10 of 61) at 90 to 100 days post-transplant.

Myeloablation and engraftment were evaluated by complete blood cell count tests daily until neutrophil and platelet engraftment, and then weekly until Day 30, and at Day 60 and Day 90-100. Myeloablation was defined as any of the following: absolute neutrophil count (ANC) < 500/mm^3, absolute lymphocyte count < 100/mm^3, or platelet count < 20,000/mm^3). Neutrophil engraftment was defined as ANC > 500/mm^3 ×3 consecutive daily assessments. Platelet engraftment was defined as untransfused platelet counts > 20,000/mm^3 ×3 consecutive daily assessments. Nonengraftment was defined as failure to reach an ANC > 500/mm^3 ×3 consecutive daily assessments by Day 90-100.

Myeloablation, neutrophil engraftment and platelet engraftment were achieved by all 61 patients. Myeloablation occurred on ASCT Day 5 (range ASCT days -1 to 6) with the median time to myeloablation from dosing of 8 days. The median time to neutrophil engraftment was 12 days (range ASCT days 10 to 16). The median time to platelet engraftment was 13 days (range ASCT days 10 to 28).

15 REFERENCES

1. OSHA Hazardous Drugs. OSHA. [Accessed on 9 December 2014, from http://www.osha.gov/SLTC/hazardousdrugs/index.html].

16 HOW SUPPLIED/STORAGE AND HANDLING

How Supplied

Evomela is supplied in a single carton containing one (1) vial. Each 50 mg vial contains a white to off- white lyophilized powder in single-dose vial for reconstitution (after reconstitution the solution is clear and coloress to light yellow). Each vial contains 50 mg melphalan free base equivalent to 56 mg melphalan hydrochloride.

NDC 72893-001-01: Individual carton of Evomela single-dose vial containing 50 mg melphalan free base.

Storage and Handling

Store Evomela at room temperature 25°C (77°F). Temperature excursions are permitted between 15- 30°C (59-86°F). [see USP Controlled Room Temperature]

Evomela is light sensitive. Retain in original carton until use.

Melphalan is a hazardous drug. Follow applicable special handling and disposal procedures.^1

17 PATIENT COUNSELING INFORMATION

Advise the patient to read the FDA-approved patient labeling (Patient Information).

Advise patients or their caregivers of the following:

Low Blood Cell Counts

- To report any signs or symptoms of thrombocytopenia, leukopenia (neutropenia and lymphopenia), and anemia. Inform patients of the need for routine blood counts [see Warnings and Precautions (5.1)].

Mucositis

- Inform patients of the signs and symptoms of mucositis. Instruct patients on ways to reduce the risk of its development, and on ways to maintain nutrition and control discomfort if it occurs [see Warnings and Precautions (5.2)].

Nausea, Vomiting and Diarrhea

- To report symptoms of nausea, vomiting and diarrhea, so that appropriate antiemetic and/or antidiarrheal medications can be administered [see Warnings and Precautions (5.2)].

Allergic Reactions

- To immediately report symptoms of hypersensitivity reactions including changes involving the skin, breathing or heart rate, so that antihistamine or corticosteroid therapy can be administered [see Warnings and Precautions (5.4)].

Secondary cancers

- To understand the potential long-term risks related to secondary malignancy [see Warnings and Precautions (5.5)].

Embryo-Fetal Toxicity

- Advise pregnant women of the potential risk to a fetus [see Warnings and Precautions (5.6) and Use in Specific Populations (8.1)].
- Advise females of reproductive potential to use effective contraception during treatment with Evomela and for 6 months after the last dose. Advise females to contact their healthcare provider if they become pregnant, or if pregnancy is suspected, while taking Evomela [see Warnings and Precautions (5.6) and Use in Specific Populations (8.1, 8.3)].
- Inform both females and males of reproductive potential about the risk for infertility [see Warnings and Precautions (5.7) and Use in Specific Populations (8.3)].
- Advise males with female partners of reproductive potential to use effective contraception during treatment with Evomela and for 3 months after the last dose [see Use in Specific Populations (8.3)].

Lactation

- Advise women not to breastfeed during treatment with Evomela and for one week after the last dose [see Use in Specific Populations (8.2)].

Manufacturer by:
Cenexi Laboratories Thissen S.A
Braine I’Alleud, 1420, Belgium
or
Manufactured by:
Baxter Oncology GmbH
Hale 33790 Germany

Manufactured for:
Acrotech Biopharma Inc.
East Windsor, NJ 08520
1-888 -292-9617

PATIENT INFORMATION

EVOMELA (ev-o-meh-lah)
(melphalan) for injection, for intravenous use

What is Evomela?

Evomela is a prescription medicine used in people with a type of cancer called multiple myeloma before receiving a stem cell transplant (conditioning treatment).

It is not known if Evomela is safe and effective in children.
Do not receive Evomela if you are allergic to melphalan or any of the ingredients in Evomela. See the end of this leaflet for a complete list of ingredients in Evomela.

Before you receive Evomela, tell your healthcare provider about all of your medical conditions, including if you:

- have an infection
- have had chemotherapy treatment
- have nausea, vomiting, or diarrhea
- have liver or kidney problems
- are pregnant or plan to become pregnant. Evomela can harm your unborn baby.

Females who can become pregnant:

o You should not become pregnant during treatment with Evomela.
o You should use effective birth control (contraception) during treatment and for 6 months after your last dose of Evomela.
o Tell your healthcare provider right away if you become pregnant or think you may be pregnant during treatment with Evomela.

Males with female partners who can become pregnant:

o You should use effective birth control (contraception) during treatment and for 3 months after your last dose of Evomela.

- are breastfeeding or plan to breastfeed. It is not known if Evomela passes into your breast milk. You should not breastfeed during treatment with Evomela.

Tell your healthcare provider about all the medicines you take, including prescription and over-the-counter medicines, vitamins, and herbal supplements.

How will I receive Evomela?

- Evomela is given to you into your vein through an intravenous (IV) line over 30 minutes.
- Your healthcare provider will do blood tests before and during your treatment with Evomela.
- Your healthcare provider will prescribe medicines to help prevent nausea.

What are the possible side effects of Evomela?
Evomela may cause serious side effects, including:

- Low blood cell counts are common with Evomela and can be serious. Your healthcare provider will do blood tests as needed to check your blood counts during your treatment with Evomela.

ᴼ Low platelet counts: Tell your healthcare provider right away if you have unusual bleeding or bruising under your skin.
ᴼ Low red blood cell counts: Tell your healthcare provider if you are feeling weak, tired, or you get tired easily, you look pale, or you feel short of breath.
ᴼ Low white blood cell counts: A low white blood cell count can cause you to get infections, which may be serious. Tell your healthcare provider right away if you have symptoms of infection, such as fever, chills, cough, pain or burning during urination.

- Redness and sores of the lining of the mouth, lips, throat, stomach, and genitals (mucositis). Mucositis is common during treatment with Evomela, and can sometimes be severe. Mucositis may cause discomfort or pain.
  Your healthcare provider will tell you about ways to maintain nutrition and help control the discomfort from mucositis, and may prescribe medicines if needed.
- Nausea, vomiting, and diarrhea are common with Evomela and can sometimes be serious. Tell your healthcare provider if you get nausea, vomiting, or diarrhea. Your healthcare provider may prescribe medicines to help prevent or treat these side effects.
- Liver problems. Your healthcare provider will check you for liver problems during treatment with Evomela. Tell your healthcare provider right away if you get any of the following signs or symptoms:
  ᴼ yellowing of your skin or the whites of your eyes
  ᴼ pain on the right side of your stomach-area (abdomen)
  ᴼ severe nausea or vomiting
  ᴼ dark urine (tea colored)

- Serious Allergic reactions. Tell your healthcare provider right away if you get any of the following signs or symptoms:
  ᴼ skin reactions, including welts, rash, itching, and redness
  ᴼ fast heartbeat
  ᴼ shortness of breath or trouble breathing
  ᴼ feel lightheaded or dizzy
  ᴼ blurry vision
  ᴼ swelling of your face, tongue, or thro
  ᴼ chest tightness
  ᴼ wheezingt

Your healthcare provider may need to discontinue treatment with Evomela if you have a serious allergic reaction.

- Secondary cancers. New cancers have happened in people who have been treated with Evomela.
- Infertility. Evomela may cause fertility problems in males and females. Talk to your healthcare provider if this is a concern for you. In females, your menstrual periods may stop due to treatment with Evomela.

The most common side effects of Evomela includetiredness and low potassium level.

These are not all the possible side effects of Evomela.

Call your doctor for medical advice about side effects. You may report side effects to FDA at 1-800-FDA-1088.

General information about the safe and effective use of Evomela.
Medicines are sometimes prescribed for purposes other than those listed in a Patient Information leaflet. You can ask your pharmacist or healthcare provider for information about Evomela that is written for health professionals.

What are the ingredients in Evomela?
Active ingredient: melphalan hydrochloride
Inactive ingredient: Betadex Sulfobutyl Ether Sodium. Sodium hydroxide and if necessary, hydrochloride acid is added as a pH adjuster.

Manufacturer by:
Cenexi Laboratories Thissen S.A
Braine I’Alleud, 1420, Belgium
or
Manufactured by:
Baxter Oncology GmbH
Hale 33790 Germany

Manufactured for:
Acrotech Biopharma Inc.
East Windsor, NJ 08520
For more information, go to www.evomela.com or call 1-888-292-9617.
This Patient Information has been approved by the U.S. Food and Drug Administration. Revised: June 2023

PACKAGE/LABEL PRINCIPAL DISPLAY PANEL

Evomela Carton Label

NDC 72893-001-01

Evomela® (melphalan) for Injection

50 mg per vial*

For Intravenous Infusion Only

Single-Use Vial

Discard Unused Portion

Sterile

*Each vial contains 50 mg melphalan free base equivalent to 56 mg melphalan hydrochloride.

Acrotech Biopharma Inc.

Evomela Vial Label

NDC 72893-001-01

Evomela® (melphalan) for Injection

50 mg per vial*

For Intravenous Infusion Only

Single-Use Vial Discard Unused Portion

Sterile

*Each vial contains 50 mg melphalan free base equivalent to 56 mg melphalan hydrochloride.

Rx only